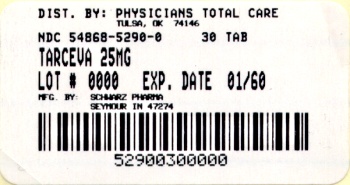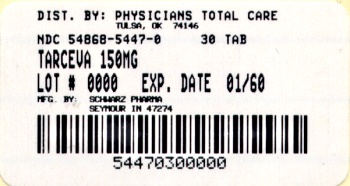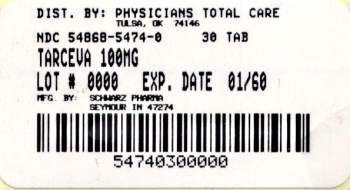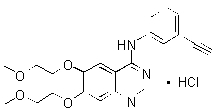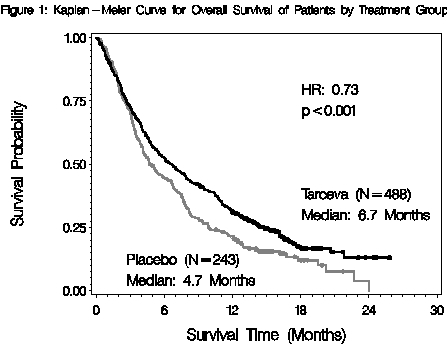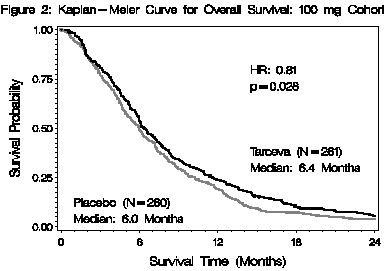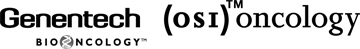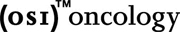 DRUG LABEL: Tarceva
NDC: 54868-5290 | Form: TABLET
Manufacturer: Physicians Total Care, Inc.
Category: prescription | Type: HUMAN PRESCRIPTION DRUG LABEL
Date: 20120105

ACTIVE INGREDIENTS: ERLOTINIB HYDROCHLORIDE 25 mg/1 1
INACTIVE INGREDIENTS: LACTOSE MONOHYDRATE; HYPROMELLOSES; HYDROXYPROPYL CELLULOSE; MAGNESIUM STEARATE; CELLULOSE, MICROCRYSTALLINE; SODIUM STARCH GLYCOLATE TYPE A POTATO; SODIUM LAURYL SULFATE; TITANIUM DIOXIDE; FD&C YELLOW NO. 6

HIGHLIGHTS OF PRESCRIBING INFORMATION

These highlights do not include all the information needed to use TARCEVA safely and effectively. See full prescribing information for TARCEVA. TARCEVA (erlotinib hydrochloride) tablet for oral use Initial U.S. Approval: 2004

RECENT MAJOR CHANGES

Warnings and Precautions, Hepatic Impairment (5.2) 09/2008

Warnings and Precautions, Hepatotoxicity (5.3) 09/2008

Warning and Precautions, Renal Failure (5.4) 09/2008

1. INDICATIONS AND USAGE

TARCEVA is a tyrosine kinase inhibitor indicated for the treatment of:

- Locally advanced or metastatic non-small cell lung cancer (NSCLC) after failure of at least one prior chemotherapy regimen. (1.1)
- First-line treatment of patients with locally advanced, unresectable or metastatic pancreatic cancer, in combination with gemcitabine. (1.2)

2. DOSAGE AND ADMINISTRATION

- The dose for NSCLC is 150 mg/day. (2.1)
- The dose for pancreatic cancer is 100 mg/day. (2.2)
- All doses of TARCEVA should be taken at least one hour before or two hours after food. (2.1, 2.2)
- Reduce in 50 mg decrements, when necessary. (2.3)

3. DOSAGE FORMS AND STRENGTHS

- Tablets: 25 mg, 100 mg and 150 mg. (3)

4. CONTRAINDICATIONS

None

5. WARNINGS AND PRECAUTIONS

- Interstitial Lung Disease (ILD)-like events, including fatalities have been infrequently reported. Interrupt TARCEVA if acute onset of new or progressive unexplained pulmonary symptoms, such as dyspnea, cough and fever occur. Discontinue TARCEVA if ILD is diagnosed. (5.1)
- Monitor patients with hepatic impairment closely. Interrupt or discontinue TARCEVA if changes in liver function are severe (5.2)
- Cases of hepatic failure and hepatorenal syndrome (including fatalities) have been reported. Monitor periodic liver function testing. Interrupt or discontinue TARCEVA if liver function changes are severe. (5.3)
- Cases of acute renal failure (including fatalities), and renal insufficiency have been reported. Interrupt TARCEVA in the event of dehydration. Monitor renal function and electrolytes in patients at risk of dehydration. (5.4)
- Myocardial infarction/ischemia has been reported, including fatalities, in patients with pancreatic cancer. (5.5)
- Cerebrovascular accidents, including a fatality, have been reported in patients with pancreatic cancer. (5.6)
- Microangiopathic Hemolytic Anemia with thrombocytopenia has been reported in patients with pancreatic cancer. (5.7)
- Women should be advised to avoid pregnancy while on TARCEVA. Treatment should only be continued if the potential benefit to the mother outweighs the risk to the fetus. (5.8)
- International Normalized Ratio (INR) elevations and bleeding events, some associated with concomitant warfarin administration have been reported. Monitor patients taking warfarin or other coumarin-derivative anticoagulants. (5.9)

6. ADVERSE REACTIONS

The most common adverse reactions (>50%) in NSCLC are rash, diarrhea, anorexia and fatigue. (6.1)

The most common adverse reactions (>50%) in pancreatic cancer are fatigue, rash, nausea and anorexia. (6.2)

To report SUSPECTED ADVERSE REACTIONS, contact OSI Pharmaceuticals Inc. at 1-800-572-1932
or FDA at 1-800-FDA-1088 or www.fda.gov/medwatch

7. DRUG INTERACTIONS

- CYP3A4 inhibitors may increase erlotinib plasma concentrations. (7)
- CYP3A4 inducers may decrease erlotinib plasma concentrations. (7)
- CYP1A2 inducers may decrease erlotinib plasma concentrations. (7)
- Erlotinib solubility is pH dependent. Drugs that alter the pH of the upper GI tract may alter the solubility of erlotinib and hence its absorption. (7)
- Cigarette smoking decreases erlotinib plasma concentrations (7)

FULL PRESCRIBING INFORMATION

RECENT MAJOR CHANGES

Enter section text here

1. INDICATIONS AND USAGE

Enter section text here

1.1 Non-Small Cell Lung Cancer (NSCLC)

TARCEVA monotherapy is indicated for the treatment of patients with locally advanced or metastatic non-small cell lung cancer after failure of at least one prior chemotherapy regimen [see Clinical Studies (14.1)].

Results from two, multicenter, placebo-controlled, randomized, Phase 3 trials conducted in first-line patients with locally advanced or metastatic NSCLC showed no clinical benefit with the concurrent administration of TARCEVA with platinum-based chemotherapy [carboplatin and paclitaxel or gemcitabine and cisplatin] and its use is not recommended in that setting [see Clinical Studies (14.3)].

1.2 Pancreatic Cancer

TARCEVA in combination with gemcitabine is indicated for the first-line treatment of patients with locally advanced, unresectable or metastatic pancreatic cancer [see Clinical Studies (14.3)].

2. DOSAGE AND ADMINISTRATION

Enter section text here

2.1 Recommended Dose - NSCLC

The recommended daily dose of TARCEVA for non-small cell lung cancer is 150 mg taken at least one hour before or two hours after the ingestion of food. Treatment should continue until disease progression or unacceptable toxicity occurs. There is no evidence that treatment beyond progression is beneficial.

2.2 Recommended Dose - Pancreatic Cancer

The recommended daily dose of TARCEVA for pancreatic cancer is 100 mg taken at least one hour before or two hours after the ingestion of food, in combination with gemcitabine (see the gemcitabine package insert). Treatment should continue until disease progression or unacceptable toxicity occurs.

2.3 Dose Modifications

In patients who develop an acute onset of new or progressive pulmonary symptoms, such as dyspnea, cough or fever, treatment with TARCEVA should be interrupted pending diagnostic evaluation. If Interstitial Lung Disease (ILD) is diagnosed, TARCEVA should be discontinued and appropriate treatment instituted as necessary [see Warnings and Precautions (5.1)].

Diarrhea can usually be managed with loperamide. Patients with severe diarrhea who are unresponsive to loperamide or who become dehydrated may require dose reduction or temporary interruption of therapy. Patients with severe skin reactions may also require dose reduction or temporary interruption of therapy.

When dose reduction is necessary, the TARCEVA dose should be reduced in 50 mg decrements.

In patients who are taking TARCEVA with a strong CYP3A4 inhibitor such as, but not limited to, atazanavir, clarithromycin, indinavir, itraconazole, ketoconazole, nefazodone, nelfinavir, ritonavir, saquinavir, telithromycin, troleandomycin (TAO), voriconazole, or grapefruit or grapefruit juice, a dose reduction should be considered if severe adverse reactions occur. Similarly, in patients who are taking TARCEVA with an inhibitor of both CYP3A4 and CYP1A2 like ciprofloxacin, a dose reduction of TARCEVA should be considered if severe adverse reactions occur. [see Drug Interactions (7)].

Pre-treatment with the CYP3A4 inducer rifampicin decreased erlotinib AUC by about 2/3 to 4/5. Use of alternative treatments lacking CYP3A4 inducing activity is strongly recommended. If an alternative treatment is unavailable, an increase in the dose of TARCEVA should be considered as tolerated at two week intervals while monitoring the patient’s safety. The maximum dose of TARCEVA studied in combination with rifampicin is 450 mg. If the TARCEVA dose is adjusted upward, the dose will need to be reduced immediately to the indicated starting dose upon discontinuation of rifampicin or other inducers. Other CYP3A4 inducers include, but are not limited to rifabutin, rifapentine, phenytoin, carbamazepine, phenobarbital and St. John's Wort. These too should be avoided if possible [see Drug Interactions (7)].

Cigarette smoking has been shown to reduce erlotinib exposure. Patients should be advised to stop smoking. If a patient continues to smoke, a cautious increase in the dose of TARCEVA, not exceeding 300 mg may be considered, while monitoring the patient’s safety. However, efficacy and long-term safety (> 14 days) of a dose higher than the recommended starting doses have not been established in patients who continue to smoke cigarettes. If the TARCEVA dose is adjusted upward, the dose should be reduced immediately to the indicated starting dose upon cessation of smoking [see Clinical Pharmacology (12.3)].

Erlotinib is eliminated by hepatic metabolism and biliary excretion. Although erlotinib exposure was similar in patients with moderately impaired hepatic function (Child-Pugh B), patients with hepatic impairment (total bilirubin > ULN or Child-Pugh A, B and C) should be closely monitored during therapy with TARCEVA [see WARNINGS and PRECAUTIONS (5.2)]. Treatment with TARCEVA should be used with extra caution in patients with total bilirubin > 3 x ULN. TARCEVA dosing should be interrupted or discontinued if changes in liver function are severe such as doubling of total bilirubin and/or tripling of transaminases in the setting of pretreatment values outside normal range. In the setting of worsening liver function tests, before they become severe, dose interruption and/or dose reduction with frequent liver function test monitoring should be considered. TARCEVA dosing should be interrupted or discontinued if total bilirubin is >3 x ULN and/or transaminases are >5 x ULN in the setting of normal pretreatment values [see Warnings and Precautions (5.2 , 5.3), Adverse Reactions (6.3) and Use in Specific Populations (8.6)].

3. DOSAGE FORMS AND STRENGTHS

25 mg tablets

White film-coated tablets for daily oral administration. Round, biconvex face and straight sides, white film-coated, printed in orange with a “T” and “25” on one side and plain on the other side.

100 mg tablets

White film-coated tablets for daily oral administration. Round, biconvex face and straight sides, white film-coated, printed in gray with “T” and “100” on one side and plain on the other side.

150 mg tablets

White film-coated tablets for daily oral administration. Round, biconvex face and straight sides, white film-coated, printed in maroon with “T” and “150” on one side and plain on the other side.

4. CONTRAINDICATIONS

None.

5. WARNINGS AND PRECAUTIONS

Enter section text here

5.1 Pulmonary Toxicity

There have been infrequent reports of serious Interstitial Lung Disease (ILD)-like events, including fatalities, in patients receiving TARCEVA for treatment of NSCLC, pancreatic cancer or other advanced solid tumors. In the randomized single-agent NSCLC study [see CLINICAL STUDIES (14.1)], the incidence of ILD-like events (0.8%) was the same in both the placebo and TARCEVA groups. In the pancreatic cancer study - in combination with gemcitabine – [see Clinical Studies (14.3)], the incidence of ILD-like events was 2.5% in the TARCEVA plus gemcitabine group vs. 0.4% in the placebo plus gemcitabine group.

The overall incidence of ILD-like events in approximately 4900 TARCEVA-treated patients from all studies (including uncontrolled studies and studies with concurrent chemotherapy) was approximately 0.7%. Reported diagnoses in patients suspected of having ILD-like events included pneumonitis, radiation pneumonitis, hypersensitivity pneumonitis, interstitial pneumonia, interstitial lung disease, obliterative bronchiolitis, pulmonary fibrosis, Acute Respiratory Distress Syndrome and lung infiltration. Symptoms started from 5 days to more than 9 months (median 39 days) after initiating TARCEVA therapy. In the lung cancer trials most of the cases were associated with confounding or contributing factors such as concomitant/prior chemotherapy, prior radiotherapy, pre-existing parenchymal lung disease, metastatic lung disease, or pulmonary infections.

In the event of an acute onset of new or progressive unexplained pulmonary symptoms such as dyspnea, cough, and fever, TARCEVA therapy should be interrupted pending diagnostic evaluation. If ILD is diagnosed, TARCEVA should be discontinued and appropriate treatment instituted as needed [see Dosage and Administration (2.3)].

5.2 Patients with Hepatic Impairment

In a pharmacokinetic study in patients with moderate hepatic impairment (Child-Pugh B) associated with significant liver tumor burden, 10 out of 15 patients died on treatment or within 30 days of the last TARCEVA dose. One patient died from hepatorenal syndrome, 1 patient died from rapidly progressing liver failure and the remaining 8 patients died from progressive disease. Six out of the 10 patients who died had baseline total bilirubin > 3 x ULN suggesting severe hepatic impairment. Treatment with TARCEVA should be used with extra caution in patients with total bilirubin > 3 x ULN. Patients with hepatic impairment (total bilirubin > ULN or Child-Pugh A, B and C) should be closely monitored during therapy with TARCEVA. TARCEVA dosing should be interrupted or discontinued if changes in liver function are severe such as doubling of total bilirubin and/or tripling of transaminases in the setting of pretreatment values outside normal range [see Clinical Pharmacology (12.3) and Dosage and Administration (2.3)].

5.3 Hepatotoxicity

Cases of hepatic failure and hepatorenal syndrome (including fatalities) have been reported during use of TARCEVA, particularly in patients with baseline hepatic impairment. Therefore, periodic liver function testing (transaminases, bilirubin, and alkaline phosphatase) is recommended. In the setting of worsening liver function tests, dose interruption and/or dose reduction with frequent liver function test monitoring should be considered. TARCEVA dosing should be interrupted or discontinued if total bilirubin is >3 x ULN and/or transaminases are >5 x ULN in the setting of normal pretreatment values [see Adverse Reactions (6.3) and Dosage and Administration (2.3)].

5.4 Renal Failure

Cases of hepatorenal syndrome, acute renal failure (including fatalities), and renal insufficiency have been reported. Some were secondary to baseline hepatic impairment while others were associated with severe dehydration due to diarrhea, vomiting, and/or anorexia or concurrent chemotherapy use. In the event of dehydration, particularly in patients with contributing risk factors for renal failure (eg, pre-existing renal disease, medical conditions or medications that may lead to renal disease, or other predisposing conditions including advanced age), TARCEVA therapy should be interrupted and appropriate measures should be taken to intensively rehydrate the patient. Periodic monitoring of renal function and serum electrolytes is recommended in patients at risk of dehydration [see Adverse Reactions (6.3) and Dosage and Administration (2.3)].

5.5 Myocardial infarction/ischemia

In the pancreatic carcinoma trial, six patients (incidence of 2.3%) in the TARCEVA/gemcitabine group developed myocardial infarction/ischemia. One of these patients died due to myocardial infarction. In comparison, 3 patients in the placebo/gemcitabine group developed myocardial infarction (incidence 1.2%) and one died due to myocardial infarction.

5.6 Cerebrovascular accident

In the pancreatic carcinoma trial, six patients in the TARCEVA/gemcitabine group developed cerebrovascular accidents (incidence: 2.3%). One of these was hemorrhagic and was the only fatal event. In comparison, in the placebo/gemcitabine group there were no cerebrovascular accidents.

5.7 Microangiopathic Hemolytic Anemia with Thrombocytopenia

In the pancreatic carcinoma trial, two patients in the TARCEVA/gemcitabine group developed microangiopathic hemolytic anemia with thrombocytopenia (incidence: 0.8%). Both patients received TARCEVA and gemcitabine concurrently. In comparison, in the placebo/gemcitabine group there were no cases of microangiopathic hemolytic anemia with thrombocytopenia.

5.8 Use in Pregnancy

Pregnancy Category D

Women of childbearing potential should avoid becoming pregnant while being treated with TARCEVA. Erlotinib administered to rabbits during organogenesis at doses that result in plasma drug concentrations of approximately 3 times those in humans (AUCs at 150 mg daily dose) was associated with embryo/fetal lethality and abortion. When erlotinib was administered to female rats prior to mating and through the first week of pregnancy, at doses 0.3 or 0.7 times the clinical dose of 150 mg, on a mg/m2 basis, there was an increase in early resorptions that resulted in a decrease in the number of live fetuses. [see Use in Specific Populations (8.1)]

5.9 Elevated International Normalized Ratio and Potential Bleeding

International Normalized Ratio (INR) elevations and infrequent reports of bleeding events including gastrointestinal and non-gastrointestinal bleedings have been reported in clinical studies, some associated with concomitant warfarin administration. Patients taking warfarin or other coumarin-derivative anticoagulants should be monitored regularly for changes in prothrombin time or INR. [see Adverse Reactions (6.3)].

6. ADVERSE REACTIONS

Because clinical trials are conducted under widely varying conditions, adverse reactions rates observed in the clinical trials of a drug cannot be directly compared to rates in the clinical trials of another drug and may not reflect the rates observed in practice.

Safety evaluation of TARCEVA is based on 856 cancer patients who received TARCEVA as monotherapy, 308 patients who received TARCEVA 100 or 150 mg plus gemcitabine, and 1228 patients who received TARCEVA concurrently with other chemotherapies.

There have been reports of serious events, including fatalities, in patients receiving TARCEVA for treatment of NSCLC, pancreatic cancer or other advanced solid tumors [see Warnings and Precautions (5) and Dosage and Administration (2.3)].

6.1 Non-Small Cell Lung Cancer

Adverse events, regardless of causality, that occurred in at least 10% of patients treated with single-agent TARCEVA at 150 mg and at least 3% more often than in the placebo group in the randomized trial of patients with NSCLC are summarized by NCI-CTC (version 2.0) Grade in Table 1.

The most common adverse reactions in patients receiving single-agent TARCEVA 150 mg were rash and diarrhea. Grade 3/4 rash and diarrhea occurred in 9% and 6%, respectively, in TARCEVA-treated patients. Rash and diarrhea each resulted in study discontinuation in 1% of TARCEVA-treated patients. Six percent and 1% of patients needed dose reduction for rash and diarrhea, respectively. The median time to onset of rash was 8 days, and the median time to onset of diarrhea was 12 days.

Table 1: Adverse Reactions Occurring More Frequently (≥ 3%) in the Single Agent TARCEVA Group than in the Placebo Group and in ≥10% of Patients in the TARCEVA Group.
 | TARCEVA 150 mg N = 485 |  |  | Placebo N = 242
NCI-CTC Grade | Any Grade | Grade 3 | Grade 4 | Any Grade | Grade 3 | Grade 4
MedDRA Preferred Term | % | % | % | % | % | %
Rash | 75 | 8 | <1 | 17 | 0 | 0
Diarrhea | 54 | 6 | <1 | 18 | <1 | 0
Anorexia | 52 | 8 | 1 | 38 | 5 | <1
Fatigue | 52 | 14 | 4 | 45 | 16 | 4
Dyspnea | 41 | 17 | 11 | 35 | 15 | 11
Cough | 33 | 4 | 0 | 29 | 2 | 0
Nausea | 33 | 3 | 0 | 24 | 2 | 0
Infection | 24 | 4 | 0 | 15 | 2 | 0
Vomiting | 23 | 2 | <1 | 19 | 2 | 0
Stomatitis | 17 | <1 | 0 | 3 | 0 | 0
Pruritus | 13 | <1 | 0 | 5 | 0 | 0
Dry skin | 12 | 0 | 0 | 4 | 0 | 0
Conjunctivitis | 12 | <1 | 0 | 2 | <1 | 0
Keratoconjunctivitis sicca | 12 | 0 | 0 | 3 | 0 | 0
Abdominal pain | 11 | 2 | <1 | 7 | 1 | <1

Liver function test abnormalities (including elevated alanine aminotransferase (ALT), aspartate aminotransferase (AST) and bilirubin) were observed in patients receiving single-agent TARCEVA 150 mg. These elevations were mainly transient or associated with liver metastases. Grade 2 (>2.5 – 5.0 x ULN) ALT elevations occurred in 4% and <1% of TARCEVA and placebo treated patients, respectively. Grade 3 (>5.0 – 20.0 x ULN) elevations were not observed in TARCEVA-treated patients. TARCEVA dosing should be interrupted or discontinued if changes in liver function are severe. [see Dosage and Administration (2.3)]

6.2 Pancreatic Cancer

Adverse events, regardless of causality, that occurred in at least 10% of patients treated with TARCEVA 100 mg plus gemcitabine in the randomized trial of patients with pancreatic cancer are summarized by NCI-CTC (version 2.0) Grade in Table 2.

The most common adverse reactions in pancreatic cancer patients receiving TARCEVA 100 mg plus gemcitabine were fatigue, rash, nausea, anorexia and diarrhea. In the TARCEVA plus gemcitabine arm, Grade 3/4 rash and diarrhea were each reported in 5% of TARCEVA plus gemcitabine-treated patients. The median time to onset of rash and diarrhea was 10 days and 15 days, respectively. Rash and diarrhea each resulted in dose reductions in 2% of patients, and resulted in study discontinuation in up to 1% of patients receiving TARCEVA plus gemcitabine. The 150 mg cohort was associated with a higher rate of certain class-specific adverse reactions including rash and required more frequent dose reduction or interruption.

Table 2: Adverse Reactions Occurring in ≥ 10% of TARCEVA-treated Pancreatic Cancer Patients: 100 mg cohort
 | TARCEVA + Gemcitabine 1000 mg/m^2 IV N=259 |  |  | Placebo + Gemcitabine 1000 mg/m^2 IV N=256
NCI-CTC Grade | Any Grade | Grade 3 | Grade 4 | Any Grade | Grade 3 | Grade 4
MedDRA Preferred Term | % | % | % | % | % | %
Fatigue | 73 | 14 | 2 | 70 | 13 | 2
Rash | 69 | 5 | 0 | 30 | 1 | 0
Nausea | 60 | 7 | 0 | 58 | 7 | 0
Anorexia | 52 | 6 | <1 | 52 | 5 | <1
Diarrhea | 48 | 5 | <1 | 36 | 2 | 0
Abdominal pain | 46 | 9 | <1 | 45 | 12 | <1
Vomiting | 42 | 7 | <1 | 41 | 4 | <1
Weight decreased | 39 | 2 | 0 | 29 | <1 | 0
Infection* | 39 | 13 | 3 | 30 | 9 | 2
Edema | 37 | 3 | <1 | 36 | 2 | <1
Pyrexia | 36 | 3 | 0 | 30 | 4 | 0
Constipation | 31 | 3 | 1 | 34 | 5 | 1
Bone pain | 25 | 4 | <1 | 23 | 2 | 0
Dyspnea | 24 | 5 | <1 | 23 | 5 | 0
Stomatitis | 22 | <1 | 0 | 12 | 0 | 0
Myalgia | 21 | 1 | 0 | 20 | <1 | 0
Depression | 19 | 2 | 0 | 14 | <1 | 0
Dyspepsia | 17 | <1 | 0 | 13 | <1 | 0
Cough | 16 | 0 | 0 | 11 | 0 | 0
Dizziness | 15 | <1 | 0 | 13 | 0 | <1
Headache | 15 | <1 | 0 | 10 | 0 | 0
Insomnia | 15 | <1 | 0 | 16 | <1 | 0
Alopecia | 14 | 0 | 0 | 11 | 0 | 0
Anxiety | 13 | 1 | 0 | 11 | <1 | 0
Neuropathy | 13 | 1 | <1 | 10 | <1 | 0
Flatulence | 13 | 0 | 0 | 9 | <1 | 0
Rigors | 12 | 0 | 0 | 9 | 0 | 0
*Includes all MedDRA preferred terms in the Infections and Infestations System Organ Class

In the pancreatic carcinoma trial, 10 patients in the TARCEVA/gemcitabine group developed deep venous thrombosis (incidence: 3.9%). In comparison, 3 patients in the placebo/gemcitabine group developed deep venous thrombosis (incidence 1.2%). The overall incidence of grade 3 or 4 thrombotic events, including deep venous thrombosis, was similar in the two treatment arms: 11% for TARCEVA plus gemcitabine and 9% for placebo plus gemcitabine.

No differences in Grade 3 or Grade 4 hematologic laboratory toxicities were detected between the TARCEVA plus gemcitabine group compared to the placebo plus gemcitabine group.

Severe adverse events (≥grade 3 NCI-CTC) in the TARCEVA plus gemcitabine group with incidences < 5% included syncope, arrhythmias, ileus, pancreatitis, hemolytic anemia including microangiopathic hemolytic anemia with thrombocytopenia, myocardial infarction/ischemia, cerebrovascular accidents including cerebral hemorrhage, and renal insufficiency [see Warnings and Precautions (5)].

Liver function test abnormalities (including elevated alanine aminotransferase (ALT), aspartate aminotransferase (AST) and bilirubin) have been observed following the administration of TARCEVA plus gemcitabine in patients with pancreatic cancer. Table 3 displays the most severe NCI-CTC grade of liver function abnormalities that developed. TARCEVA dosing should be interrupted or discontinued if changes in liver function are severe [see Dosage and Administration (2.3)].

Table 3: Liver Function Test Abnormalities (most severe NCI-CTC grade) in Pancreatic Cancer Patients: 100 mg Cohort
 | TARCEVA + Gemcitabine 1000 mg/m^2 IV N = 259 |  |  | Placebo + Gemcitabine 1000 mg/m^2 IV N = 256
NCI-CTC Grade | Grade 2 | Grade 3 | Grade 4 | Grade 2 | Grade 3 | Grade 4
Bilirubin | 17 % | 10% | <1% | 11% | 10% | 3%
ALT | 31% | 13% | <1% | 22% | 9% | 0%
AST | 24% | 10% | <1% | 19% | 9% | 0%

6.3 NSCLC and Pancreatic Cancer Indications

During the NSCLC and the combination pancreatic cancer trials, infrequent cases of gastrointestinal bleeding have been reported, some associated with concomitant warfarin or NSAID administration. [see Warnings and Precautions (5.9)]. These adverse events were reported as peptic ulcer bleeding (gastritis, gastroduodenal ulcers), hematemesis, hematochezia, melena and hemorrhage from possible colitis. Cases of acute renal failure or renal insufficiency, including fatalities, with or without hypokalemia have been reported. [see Warnings and Precautions (5.4)]. Cases of Grade 1 epistaxis were also reported in both the single-agent NSCLC and the pancreatic cancer clinical trials.

NCI-CTC Grade 3 conjunctivitis and keratitis have been reported infrequently in patients receiving TARCEVA therapy in the NSCLC and pancreatic cancer clinical trials. Corneal ulcerations may also occur. [see Patient Counseling Information (17)].

Hair and nail disorders including alopecia, hirsutism, eyelash/eyebrow changes, paronychia and brittle and loose nails have been reported in clinical trials and during post-marketing use of TARCEVA.

In patients who develop skin rash, the appearance of the rash is typically erythematous and maculopapular and it may resemble acne with follicular pustules, but is histopathologically different. This skin reaction commonly occurs on the face, upper chest and back, but may be more generalized or severe (NCI-CTC Grade 3 or 4) with desquamation. Associated symptoms may include itching, tenderness and/or burning. Dry skin with or without digital skin fissures may occur.

Hepatic failure has been reported in patients treated with single-agent TARCEVA or TARCEVA combined with chemotherapy in clinical studies and during post-marketing use of TARCEVA [see Warnings and Precautions (5.3)]; it is not possible to reliably estimate the frequency or establish a causal relationship to TARCEVA treatment.

In general, no notable differences in the safety of TARCEVA monotherapy or in combination with gemcitabine could be discerned between females or males and between patients younger or older than the age of 65 years [see Use in Specific Populations (8.4)]. The safety of TARCEVA appears similar in Caucasian and Asian patients.

7. DRUG INTERACTIONS

Erlotinib is metabolized predominantly by CYP3A4, and inhibitors of CYP3A4 would be expected to increase exposure. Co-treatment with the potent CYP3A4 inhibitor ketoconazole increases erlotinib AUC by 2/3. When TARCEVA was co-administered with ciprofloxacin, an inhibitor of both CYP3A4 and CYP1A2, the erlotinib exposure [AUC] and maximum concentration [Cmax] increased by 39% and 17% respectively. Caution should be used when administering or taking TARCEVA with ketoconazole and other strong CYP3A4 inhibitors such as, but not limited to, atazanavir, clarithromycin, indinavir, itraconazole, nefazodone, nelfinavir, ritonavir, saquinavir, telithromycin, troleandomycin (TAO), voriconazole and grapefruit or grapefruit juice. [see Dosage and Administration (2.3)].

Pre-treatment with the CYP3A4 inducer rifampicin for 7 days prior to TARCEVA decreased erlotinib AUC by about 2/3 to 4/5, which is equivalent to a dose of about 30 to 50 mg in NSCLC patients. In a separate study, treatment with rifampicin for 11 days, with co-administration of a single 450 mg dose of TARCEVA on day 8 resulted in a mean erlotinib exposure (AUC) that was 57.6% of that observed following a single 150 mg TARCEVA dose in the absence of rifampicin treatment [see Dose Modifications (2.3)]. Use of alternative treatments lacking CYP3A4 inducing activity is strongly recommended. If an alternative treatment is unavailable, adjusting the starting dose should be considered. If the TARCEVA dose is adjusted upward, the dose will need to be reduced immediately to the indicated starting dose upon discontinuation of rifampicin or other inducers. Other CYP3A4 inducers include, but are not limited to, rifabutin, rifapentine, phenytoin, carbamazepine, phenobarbital and St. John's Wort [see Dosage and Administration (2.3)].

Cigarette smoking has been shown to reduce erlotinib AUC. Patients should be advised to stop smoking; however, if they continue to smoke, a cautious increase in the dose of TARCEVA may be considered, while monitoring the patient’s safety. If the TARCEVA dose is adjusted upward, the dose should be reduced immediately to the indicated starting dose upon cessation of smoking. [see Dosage and Administration(2.3) and Clinical Pharmacology(12.3)].

Pretreatment and co-administration of TARCEVA decreased the AUC of CYP3A4 substrate, midazolam, by 24%. The mechanism is not clear.

In a study, there were no significant effects of gemcitabine on the pharmacokinetics of erlotinib nor were there significant effects of erlotinib on the pharmacokinetics of gemcitabine.

Drugs that alter the pH of the upper GI tract may alter the solubility of erlotinib and reduce its bioavailability. Co-administration of TARCEVA with omeprazole, a proton pump inhibitor, decreased the erlotinib AUC by 46%. Increasing the dose of TARCEVA when co-administered with such agents is not likely to compensate for the loss of exposure. Since proton pump inhibitors affect pH of the upper GI tract for an extended period, separation of doses may not eliminate the interaction. The concomitant use of proton pump inhibitors with TARCEVA should be avoided if possible. The use of antacids may be considered in place of histamine 2 receptor blockers (H2 blockers) or proton pump inhibitors in patients receiving TARCEVA. However, no clinical study has been conducted to evaluate the effect of antacids on erlotinib pharmacokinetics. If an antacid is necessary, the antacid dose and the TARCEVA dose should be separated by several hours [see Clinical Pharmacology (12.3)].

8. USE IN SPECIFIC POPULATIONS

8.1 Pregnancy

Pregnancy Category D [See Warnings and Precautions (5.8)]

Erlotinib has been shown to cause maternal toxicity with associated embryo/fetal lethality and abortion in rabbits when given at doses that result in plasma drug concentrations of approximately 3 times those in humans (AUCs at 150 mg daily dose). When given during the period of organogenesis to achieve plasma drug concentrations approximately equal to those in humans, based on AUC, there was no increased incidence of embryo/fetal lethality or abortion in rabbits or rats. However, female rats treated with 30 mg/m^2/day or 60 mg/m^2/day (0.3 or 0.7 times the clinical dose, on a mg/m^2 basis) of erlotinib prior to mating through the first week of pregnancy had an increase in early resorptions that resulted in a decrease in the number of live fetuses.

No teratogenic effects were observed in rabbits or rats dosed with erlotinib during organogenesis at doses up to 600 mg/m^2/day in the rabbit (3 times the plasma drug concentration seen in humans at 150 mg/day) and up to 60 mg/m^2/day in the rat (0.7 times the clinical dose of 150 mg/day on a mg/m^2 basis).

There are no adequate and well-controlled studies in pregnant women using TARCEVA. Women of childbearing potential should be advised to avoid pregnancy while on TARCEVA. Adequate contraceptive methods should be used during therapy, and for at least 2 weeks after completing therapy. Treatment should only be continued in pregnant women if the potential benefit to the mother outweighs the risk to the fetus. If TARCEVA is used during pregnancy, the patient should be apprised of the potential hazard to the fetus or potential risk for loss of the pregnancy [see Warnings and Precautions (5.8)].

8.3 Nursing Mothers

It is not known whether erlotinib is excreted in human milk. Because many drugs are excreted in human milk and because of the potential for serious adverse reactions in nursing infants from TARCEVA, a decision should be made whether to discontinue nursing or discontinue the drug, taking into account the importance of the drug to the mother.

8.4 Pediatric Use

The safety and effectiveness of TARCEVA in pediatric patients have not been established.

8.5 Geriatric Use

Of the total number of patients participating in the randomized NSCLC trial, 62% were less than 65 years of age, and 38% of patients were aged 65 years or older. The survival benefit was maintained across both age groups [HR = 0.75 (95% CI: 0.6, 0.9) in patients less than 65 years of age, and HR = 0.79 (95% CI: 0.6, 1.0) in patients who were 65 years or older].

In the pancreatic cancer study, 53% of patients were younger than 65 years of age and 47% were 65 years of age or older. There were no clinically relevant differences between the age groups [HR = 0.78 (95% CI: 0.6, 1.0) in patients less than 65 years of age, and HR = 0.94 (95% CI: 0.7, 1.2) in patients who were 65 years or older]. No meaningful differences in safety or pharmacokinetics were observed between younger and older patients in either study. Therefore, no dosage adjustments are recommended in elderly patients.

8.6 Gender

Of the total number of patients participating in the randomized NSCLC trial, 65% were males and 35% females. There were no clinically relevant differences in safety and efficacy based on gender [HR = 0.76 (95% CI: 0.6, 0.9) in males and HR = 0.80 (95% CI: 0.6, 1.1) in females].

In the pancreatic cancer study, 52% of patients were males and 48% females. There were no clinically relevant differences in safety and efficacy based on gender [HR = 0.74 (95% CI: 0.6, 0.9) in males and HR = 1.0 (95% CI: 0.8, 1.3) in females].

8.7 Race

In the randomized NSCLC trial, 78% of all patients were Caucasian and 12% were Asian. There were no clinically relevant differences in safety and efficacy based on race [HR = 0.79 (95% CI: 0.6, 1.0) in Caucasians and HR = 0.61 (95% CI: 0.4, 1.0) in Asians].

In the pancreatic cancer study, 88% of all patients were Caucasian and 7% were Asian. There were no clinically relevant differences in safety and efficacy based on race [HR = 0.88 (95% CI: 0.7, 1.1) in Caucasians and HR = 0.61 (95% CI: 0.3, 1.3) in Asians].

8.8 Patients with Hepatic Impairment

Patients with hepatic impairment (total bilirubin > ULN or Child Pugh A, B and C) should be closely monitored during therapy with TARCEVA. Treatment with TARCEVA should be used with extra caution in patients with total bilirubin > 3 x ULN [see Warnings (5.2), Adverse Reactions (6.3), and Dosage and Administration (2.3)].

In vitro and in vivo evidence suggest that erlotinib is cleared primarily by the liver. However, erlotinib exposure was similar in patients with moderately impaired hepatic function (Child-Pugh B) compared with patients with adequate hepatic function including patients with primary liver cancer or hepatic metastases [see Dosage and Administration (2.3) and Clinical Pharmacology (12.3)].

8.9 Patients with Renal Impairment

Less than 9% of a single dose is excreted in the urine. No clinical studies have been conducted in patients with compromised renal function.

10. OVERDOSAGE

Single oral doses of TARCEVA up to 1,000 mg in healthy subjects and weekly doses up to 1,600 mg in cancer patients have been tolerated. Repeated twice-daily doses of 200 mg single-agent TARCEVA in healthy subjects were poorly tolerated after only a few days of dosing. Based on the data from these studies, an unacceptable incidence of severe adverse events, such as diarrhea, rash, and liver transaminase elevation, may occur above the recommended dose [see Dosage and Administration (2)]. In case of suspected overdose, TARCEVA should be withheld and symptomatic treatment instituted.

11. DESCRIPTION

TARCEVA (erlotinib), a kinase inhibitor, is a quinazolinamine with the chemical name N-(3-ethynylphenyl)-6,7-bis(2-methoxyethoxy)-4-quinazolinamine. TARCEVA contains erlotinib as the hydrochloride salt that has the following structural formula:

Erlotinib hydrochloride has the molecular formula C22H23N3O4.HCl and a molecular weight of 429.90. The molecule has a pKa of 5.42 at 25oC. Erlotinib hydrochloride is very slightly soluble in water, slightly soluble in methanol and practically insoluble in acetonitrile, acetone, ethyl acetate and hexane.

Aqueous solubility of erlotinib hydrochloride is dependent on pH with increased solubility at a pH of less than 5 due to protonation of the secondary amine. Over the pH range of 1.4 to 9.6, maximal solubility of approximately 0.4 mg/mL occurs at a pH of approximately 2.

TARCEVA tablets for oral administration are available in three dosage strengths containing erlotinib hydrochloride (27.3 mg, 109.3 mg and 163.9 mg) equivalent to 25 mg, 100 mg and 150 mg erlotinib and the following inactive ingredients: lactose monohydrate, hypromellose, hydroxypropyl cellulose, magnesium stearate, microcrystalline cellulose, sodium starch glycolate, sodium lauryl sulfate and titanium dioxide. The tablets also contain trace amounts of color additives, including FD&C Yellow #6 (25 mg only) for product identification.

12. CLINICAL PHARMACOLOGY

12.1 Mechanism of Action

The mechanism of clinical antitumor action of erlotinib is not fully characterized. Erlotinib inhibits the intracellular phosphorylation of tyrosine kinase associated with the epidermal growth factor receptor (EGFR). Specificity of inhibition with regard to other tyrosine kinase receptors has not been fully characterized. EGFR is expressed on the cell surface of normal cells and cancer cells.

12.3 Pharmacokinetics

Absorption and Distribution:

Erlotinib is about 60% absorbed after oral administration and its bioavailability is substantially increased by food to almost 100%. Peak plasma levels occur 4 hours after dosing. The solubility of erlotinib is pH dependent. Erlotinib solubility decreases as pH increases. Co-administration of TARCEVA with omeprazole, a proton pump inhibitor, decreased the erlotinib exposure [AUC] and maximum concentration [Cmax] by 46% and 61% respectively [see Drug Interactions (7)].

Following absorption, erlotinib is approximately 93% protein bound to plasma albumin and alpha-1 acid glycoprotein (AAG). Erlotinib has an apparent volume of distribution of 232 liters.

Metabolism and Excretion:

A population pharmacokinetic analysis in 591 patients receiving single-agent TARCEVA showed a median half-life of 36.2 hours. Time to reach steady state plasma concentration would therefore be 7 – 8 days. No significant relationships of clearance to covariates of patient age, body weight or gender were observed. Smokers had a 24% higher rate of erlotinib clearance.

A second population pharmacokinetic analysis was conducted that incorporated erlotinib data from 204 pancreatic cancer patients who received erlotinib plus gemcitabine. This analysis demonstrated that covariates affecting erlotinib clearance in patients from the pancreatic study were very similar to those seen in the prior single-agent pharmacokinetic analysis. No new covariate effects were identified. Co-administration of gemcitabine had no effect on erlotinib plasma clearance.

In vitro assays of cytochrome P450 metabolism showed that erlotinib is metabolized primarily by CYP3A4 and to a lesser extent by CYP1A2, and the extrahepatic isoform CYP1A1. Following a 100 mg oral dose, 91% of the dose was recovered: 83% in feces (1% of the dose as intact parent) and 8% in urine (0.3% of the dose as intact parent).

Cigarette smoking reduces erlotinib exposure. In the Phase 3 NSCLC trial, current smokers achieved erlotinib steady-state trough plasma concentrations which was approximately 2-fold less than the former smokers or patients who had never smoked. This effect was accompanied by a 24% increase in apparent erlotinib plasma clearance. In a separate study which evaluated the single-dose pharmacokinetics of erlotinib in healthy volunteers, current smokers cleared the drug faster than former smokers or volunteers who had never smoked. The AUC0-infinity in smokers was about 1/3 to 1/2 of that in never/former smokers. In another study which was conducted in NSCLC patients (N=35) who were current smokers, pharmacokinetic analyses at steady-state indicated a dose-proportional increase in erlotinib exposure when the TARCEVA dose was increased from 150 mg to 300 mg. However, the exact dose to be recommended for patients who currently smoke is unknown [see Drug Interactions (7) and Patient Counseling Information (17)].

Special Populations:

Patients with Hepatic Impairment

Patients with hepatic impairment (total bilirubin > ULN or Child Pugh A, B and C) should be closely monitored during therapy with TARCEVA. Treatment with TARCEVA should be used with extra caution in patients with total bilirubin > 3 x ULN [see Warnings and Precautions (5.2), Adverse Reactions (6.3), and Dosage and Administration (2.3)].

In vitro and in vivo evidence suggest that erlotinib is cleared primarily by the liver. However, erlotinib exposure was similar in patients with moderately impaired hepatic function (Child-Pugh B) compared with patients with adequate hepatic function including patients with primary liver cancer or hepatic metastases.

Patients with Renal Impairment

Less than 9% of a single dose is excreted in the urine. No clinical studies have been conducted in patients with compromised renal function.

13. NONCLINICAL TOXICOLOGY

13.1 Carcinogenesis, Mutagenesis, Impairment of Fertility

Erlotinib has not been tested for carcinogenicity.

Erlotinib has been tested for genotoxicity in a series of in vitro assays (bacterial mutation, human lymphocyte chromosome aberration, and mammalian cell mutation) and an in vivo mouse bone marrow micronucleus test and did not cause genetic damage.

Erlotinib did not impair fertility in either male or female rats.

14. CLINICAL STUDIES

14.1 Non-Small Cell Lung Cancer NSCLC – TARCEVA Administered as a Single Agent

The efficacy and safety of single-agent TARCEVA was assessed in a randomized, double blind, placebo-controlled trial in 731 patients with locally advanced or metastatic NSCLC after failure of at least one chemotherapy regimen. Patients were randomized 2:1 to receive TARCEVA 150 mg or placebo (488 Tarceva, 243 placebo) orally once daily until disease progression or unacceptable toxicity. Study endpoints included overall survival, response rate, and progression-free survival (PFS). Duration of response was also examined. The primary endpoint was survival. The study was conducted in 17 countries.

Table 4 summarizes the demographic and disease characteristics of the study population. Demographic characteristics were well balanced between the two treatment groups. About two-thirds of the patients were male. Approximately one-fourth had a baseline ECOG performance status (PS) of 2, and 9% had a baseline ECOG PS of 3. Fifty percent of the patients had received only one prior regimen of chemotherapy. About three quarters of these patients were known to have smoked at some time.

Table 4: Demographic and Disease Characteristics
 | TARCEVA (N = 488) |  | Placebo (N = 243)
Characteristics | n | (%) | n | (%)
Gender
Female | 173 | (35) | 83 | (34)
Male | 315 | (65) | 160 | (66)
Age (years)
< 65 | 299 | (61) | 153 | (63)
≥ 65 | 189 | (39) | 90 | (37)
Race
Caucasian | 379 | (78) | 188 | (77)
Black | 18 | (4) | 12 | (5)
Asian | 63 | (13) | 28 | (12)
Other | 28 | (6) | 15 | (6)
ECOG Performance Status at Baseline*
0 | 64 | (13) | 34 | (14)
1 | 256 | (52) | 132 | (54)
2 | 126 | (26) | 56 | (23)
3 | 42 | (9) | 21 | (9)
Weight Loss in Previous 6 Months
< 5% | 320 | (66) | 166 | (68)
5 – 10% | 96 | (20) | 36 | (15)
> 10% | 52 | (11) | 29 | (12)
Unknown | 20 | (4) | 12 | (5)
Smoking History
Never Smoked | 104 | (21) | 42 | (17)
Current or Ex-smoker | 358 | (73) | 187 | (77)
Unknown | 26 | (5) | 14 | (6)
Histological Classification
Adenocarcinoma | 246 | (50) | 119 | (49)
Squamous | 144 | (30) | 78 | (32)
Undifferentiated Large Cell | 41 | (8) | 23 | (9)
Mixed Non-Small Cell | 11 | (2) | 2 | (<1)
Other | 46 | (9) | 21 | (9)
Time from Initial Diagnosis to Randomization (Months)
< 6 | 63 | (13) | 34 | (14)
6 – 12 | 157 | (32) | 85 | (35)
> 12 | 268 | (55) | 124 | (51)
Best Response to Prior Therapy at Baseline*
CR/PR | 196 | (40) | 96 | (40)
PD | 101 | (21) | 51 | (21)
SD | 191 | (39) | 96 | (40)
Number of Prior Regimens at Baseline*
1 | 243 | (50) | 121 | (50)
2 | 238 | (49) | 119 | (49)
3 | 7 | (1) | 3 | (1)
Exposure to Prior Platinum at Baseline*
Yes | 454 | (93) | 224 | (92)
No | 34 | (7) | 19 | (8)
* Stratification factor as documented at baseline; distribution differs slightly from values reported at time of randomization.

The results of the study are shown in Table 5.

Table 5: Efficacy Results
 | TARCEVA | Placebo | Hazard Ratio () | 95% CI | p-value
Survival | Median; 6.7 mo | Median; 4.7 mo | 0.73 | 0.61 – 0.86 | <0.001 ([Two-sided Log-Rank test stratified by ECOG performance status, number of prior regimens, prior platinum, best response to prior chemotherapy.])
1-year Survival | 31.2% | 21.5%
Progression-Free Survival | Median; 9.9 wk | Median; 7.9 wk | 0.59 | 0.50 – 0.70 | <0.001 ()
Tumor Response (CR+PR) | 8.9% | 0.9% |  |  | <0.001 ()
Response Duration | Median 34.3 wk | Median 15.9 wk

Survival was evaluated in the intent-to-treat population. Figure 1 depicts the Kaplan-Meier curves for overall survival. The primary survival and PFS analyses were two-sided Log-Rank tests stratified by ECOG performance status, number of prior regimens, prior platinum, best response to prior chemotherapy.

Note: HR is from Cox regression model with the following covariates: ECOG performance status, number of prior regimens, prior platinum, best response to prior chemotherapy. P-value is from two-sided Log-Rank test stratified by ECOG performance status, number of prior regimens, prior platinum, best response to prior chemotherapy.

14.2 NSCLC - TARCEVA Administered Concurrently with Chemotherapy

Results from two, multicenter, placebo-controlled, randomized, trials in over 1000 patients conducted in first-line patients with locally advanced or metastatic NSCLC showed no clinical benefit with the concurrent administration of TARCEVA with platinum-based chemotherapy [carboplatin and paclitaxel (TARCEVA, N = 526) or gemcitabine and cisplatin (TARCEVA, N = 580)].

14.3 Pancreatic Cancer - TARCEVA Administered Concurrently with Gemcitabine

The efficacy and safety of TARCEVA in combination with gemcitabine as a first-line treatment was assessed in a randomized, double blind, placebo-controlled trial in 569 patients with locally advanced, unresectable or metastatic pancreatic cancer. Patients were randomized 1:1 to receive TARCEVA (100 mg or 150 mg) or placebo once daily on a continuous schedule plus gemcitabine IV (1000 mg/m^2, Cycle 1 - Days 1, 8, 15, 22, 29, 36 and 43 of an 8 week cycle; Cycle 2 and subsequent cycles - Days 1, 8 and 15 of a 4 week cycle [the approved dose and schedule for pancreatic cancer, see the gemcitabine package insert]). TARCEVA or placebo was taken orally once daily until disease progression or unacceptable toxicity. The primary endpoint was survival. Secondary endpoints included response rate, and progression-free survival (PFS). Duration of response was also examined. The study was conducted in 18 countries. A total of 285 patients were randomized to receive gemcitabine plus TARCEVA (261 patients in the 100 mg cohort and 24 patients in the 150 mg cohort) and 284 patients were randomized to receive gemcitabine plus placebo (260 patients in the 100 mg cohort and 24 patients in the 150 mg cohort). Too few patients were treated in the 150 mg cohort to draw conclusions.

Table 6 summarizes the demographic and disease characteristics of the study population that was randomized to receive 100 mg of TARCEVA plus gemcitabine or placebo plus gemcitabine. Baseline demographic and disease characteristics of the patients were similar between the 2 treatment groups, except for a slightly larger proportion of females in the TARCEVA arm (51%) compared with the placebo arm (44%). The median time from initial diagnosis to randomization was approximately 1.0 month. Most patients presented with metastatic disease at study entry as the initial manifestation of pancreatic cancer.

Table 6: Demographic and Disease Characteristics: 100 mg Cohort
 | TARCEVA+ Gemcitabine (N=261) |  | Placebo + Gemcitabine (N=260)
Characteristics | n | (%) | n | (%)
Gender
Female | 134 | (51) | 114 | (44)
Male | 127 | (49) | 146 | (56)
Age (Years)
<65 | 136 | (52) | 138 | (53)
≥65 | 125 | (48) | 122 | (47)
Race
Caucasian | 225 | (86) | 231 | (89)
Black | 8 | (3) | 5 | (2)
Asian | 20 | (8) | 14 | (5)
Other | 8 | (3) | 10 | (3)
ECOG Performance Status*
0 | 82 | (31) | 83 | (32)
1 | 134 | (51) | 132 | (51)
2 | 44 | (17) | 45 | (17)
Unknown* | 1 | (<1) | 0 | (0)
Disease Status at Baseline**
Locally Advanced | 61 | (23) | 63 | (24)
Distant Metastasis | 200 | (77) | 197 | (76)
*Unknown includes responses of 'Unknown' and missing.
**Stratification factor as documented at baseline; distribution differs slightly from values reported at time of randomization.

The results of the study are shown in Table 7.

Table 7: Efficacy Results: 100 mg Cohort
 | TARCEVA + Gemcitabine | Placebo+ Gemcitabine | Hazard Ratio () | 95% CI | p-value
Survival | Median; 6.4 mo; 250 deaths | Median; 6.0 mo; 254 deaths | 0.81 | 0.68 – 0.97 | 0.028 ([Two-sided Log-Rank test stratified by ECOG performance status and extent of disease.])
1-year Survival | 23.8% | 19.4%
Progression-Free Survival | Median; 3.8 mo; 225 events | Median; 3.5 mo; 232 events | 0.76 | 0.64 – 0.92 | 0.006 ()
Tumor Response (CR+PR) | 8.6% | 7.9% |  |  | 0.87 ()
Response Duration | Median; 23.9 wk | Median; 23.3 wk

Survival was evaluated in the intent-to-treat population. Figure 2 depicts the Kaplan-Meier curves for overall survival in the 100 mg cohort. The primary survival and PFS analyses were two-sided Log-Rank tests stratified by ECOG performance status and extent of disease.

Note: HR is from Cox regression model with the following covariates: ECOG performance status and extent of disease. P-value is from two-sided Log-Rank test stratified by ECOG performance status and extent of disease.

16. HOW SUPPLIED/STORAGE AND HANDLING

25 mg Tablets

Round, biconvex face and straight sides, white film-coated, printed in orange with a “T” and “25” on one side and plain on the other side; supplied in:

Bottles of 30 | NDC 54868-5290-0

100 mg Tablets

Round, biconvex face and straight sides, white film-coated, printed in gray with “T” and “100” on one side and plain on the other side; supplied in:

Bottles of 30 | NDC 54868-5474-0

150 mg Tablets

Round, biconvex face and straight sides, white film-coated, printed in maroon with “T” and “150” on one side and plain on the other side; supplied in:

Bottles of 30 | NDC 54868-5447-0

Store at 25°C (77°F); excursions permitted to 15° – 30°C (59° – 86°F). See USP Controlled Room Temperature.

17. PATIENT COUNSELING INFORMATION

If the following signs or symptoms occur, patients should be advised to seek medical advice promptly [see Warnings and Precautions (5), Adverse Reactions (6) and Dosage and Administration(2.3)].

- Onset or worsening of skin rash
- Severe or persistent diarrhea, nausea, anorexia, or vomiting
- Onset or worsening of unexplained shortness of breath or cough
- Eye irritation

Given that skin reactions are anticipated when taking TARCEVA, proactive intervention may include alcohol-free emollient cream and sunscreen and the management of rash should be discussed with the patient. This may include topical corticosteroids or antibiotics with anti-inflammatory properties. These approaches were used in the NSCLC and pancreatic pivotal clinical trials. Acne preparations with drying properties may aggravate the dry skin and erythema. Treatment of rash has not been formally studied and should be based on rash severity.

Women of childbearing potential should be advised to avoid becoming pregnant while taking TARCEVA [see Warnings and Precautions (5.8) and Use in Specific Populations (8.1)].

Smokers should be advised to stop smoking while taking TARCEVA as plasma concentrations of erlotinib are reduced due to the effect of cigarette smoking [see Clinical Pharmacology (12.3)].

Manufactured for:

OSI Pharmaceuticals Inc., Melville, NY 11747

Manufactured by:

Schwarz Pharma Manufacturing, Seymour, IN 47274

Distributed by:

Genentech USA, Inc., 1 DNA Way, South San Francisco, CA 94080-4990

For further information please call 1-877-TARCEVA (1-877-827-2382).

TARCEVA and

are trademarks of OSI Pharmaceuticals, Inc., Melville, NY, 11747, USA.

©2008 OSI Pharmaceuticals, Inc., and Genentech, Inc. All rights reserved.

Additional bar code label applied by:

Physicians Total Care, Inc.
Tulsa, Oklahoma 74146

PRINCIPAL DISPLAY PANEL - PACKAGE LABEL

TARCEVA (erlotinib hydrochloride) tablet

25 mg

100 mg

150 mg